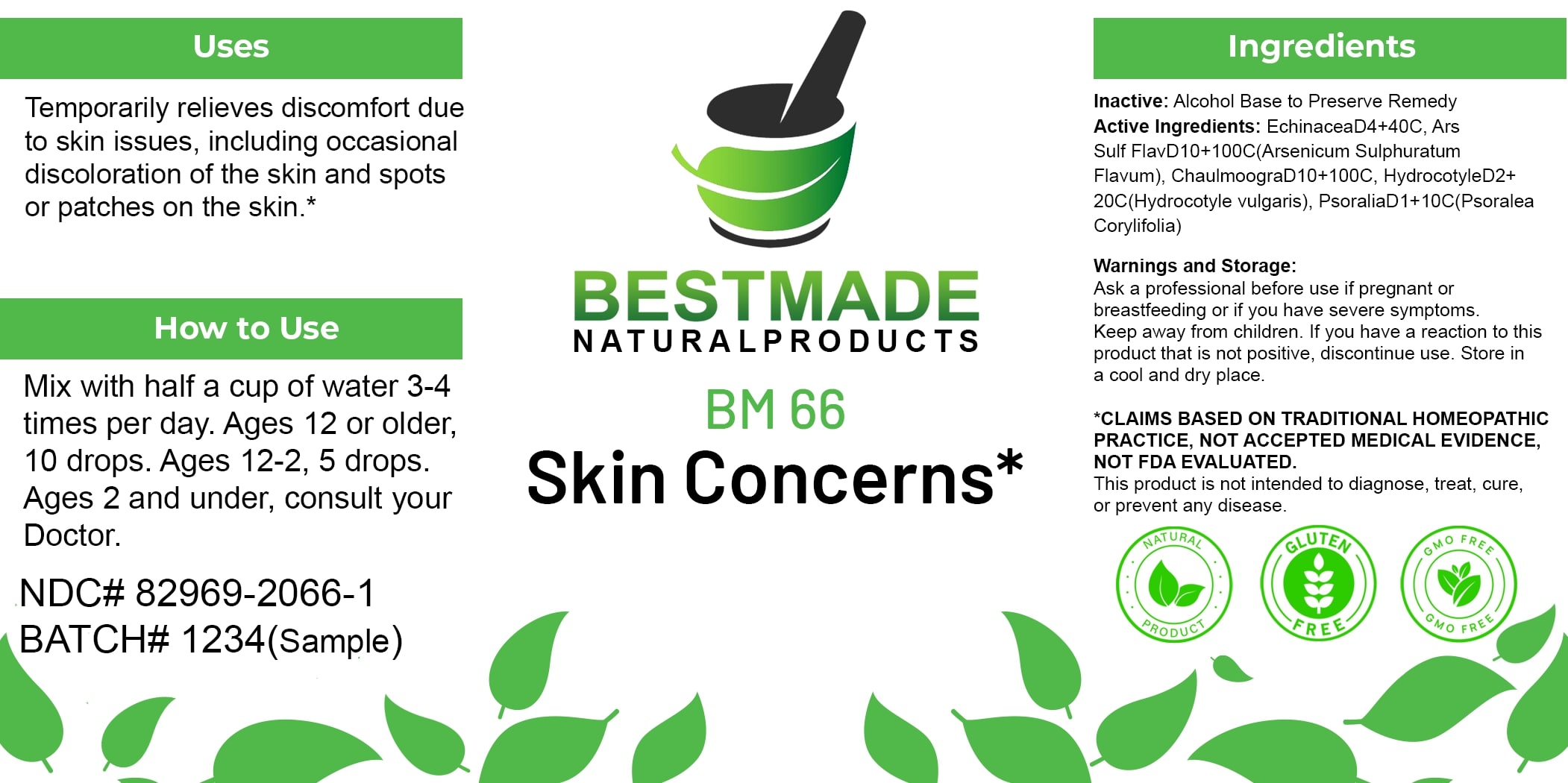 DRUG LABEL: Bestmade Natural Products BM66
NDC: 82969-2066 | Form: LIQUID
Manufacturer: Bestmade Natural Products
Category: homeopathic | Type: HUMAN OTC DRUG LABEL
Date: 20250130

ACTIVE INGREDIENTS: HYDNOCARPUS CASTANEUS WHOLE 30 [hp_C]/30 [hp_C]; CULLEN CORYLIFOLIUM WHOLE 30 [hp_C]/30 [hp_C]; CENTELLA ASIATICA 30 [hp_C]/30 [hp_C]; ECHINACEA, UNSPECIFIED 30 [hp_C]/30 [hp_C]; ARSENIC TRISULFIDE 30 [hp_C]/30 [hp_C]
INACTIVE INGREDIENTS: ALCOHOL 30 [hp_C]/30 [hp_C]

BM66

DOSAGE AND ADMINISTRATION

How to Use

Mix with half a cup of water 3-4 times per day. Ages 12 or older, 10 drops. Ages 12-2, 5 drops. Ages 2 and under, consult your Doctor.

INACTIVE INGREDIENT

Ingredients

Inactive: Alcohol Base to Preserve Remedy

ACTIVE INGREDIENT

Active Ingredients: EchinaceaD4+40C, Ars Sulf FlavD10+100C(Arsenicum Sulphuratum Flavum), ChaulmoograD10+100C, HydrocotyleD2+20C(Hydrocotyle vulgare), PsoraliaD1+10C(Psoralea Corylifolia)

Uses

Temporarily relieves discomfort due to skin issues, including occasional discoloration of the skin and spots or patches on the skin.*

*CLAIMS BASED ON TRADITIONAL HOMEOPATHIC PRACTICE, NOT ACCEPTED MEDICAL EVIDENCE, NOT FDA EVALUATED.

This product is not intended to diagnose, treat, cure, or prevent any disease.

Uses

Temporarily relieves discomfort due to skin issues, including occasional discoloration of the skin and spots or patches on the skin.*

*CLAIMS BASED ON TRADITIONAL HOMEOPATHIC PRACTICE, NOT ACCEPTED MEDICAL EVIDENCE, NOT FDA EVALUATED.

This product is not intended to diagnose, treat, cure, or prevent any disease.

KEEP OUT OF REACH OF CHILDREN

Warnings and Storage:

Ask a professional before use if pregnant or breastfeeding or if you have severe symptoms. Keep away from children. If you have a reaction to this product that is not positive, discontinue use. Store in a cool and dry place.

Warnings and Storage:

Ask a professional before use if pregnant or breastfeeding or if you have severe symptoms. Keep away from children. If you have a reaction to this product that is not positive, discontinue use. Store in a cool and dry place.

*CLAIMS BASED ON TRADITIONAL HOMEOPATHIC PRACTICE, NOT ACCEPTED MEDICAL EVIDENCE, NOT FDA EVALUATED.

This product is not intended to diagnose, treat, cure, or prevent any disease.

Entire package label